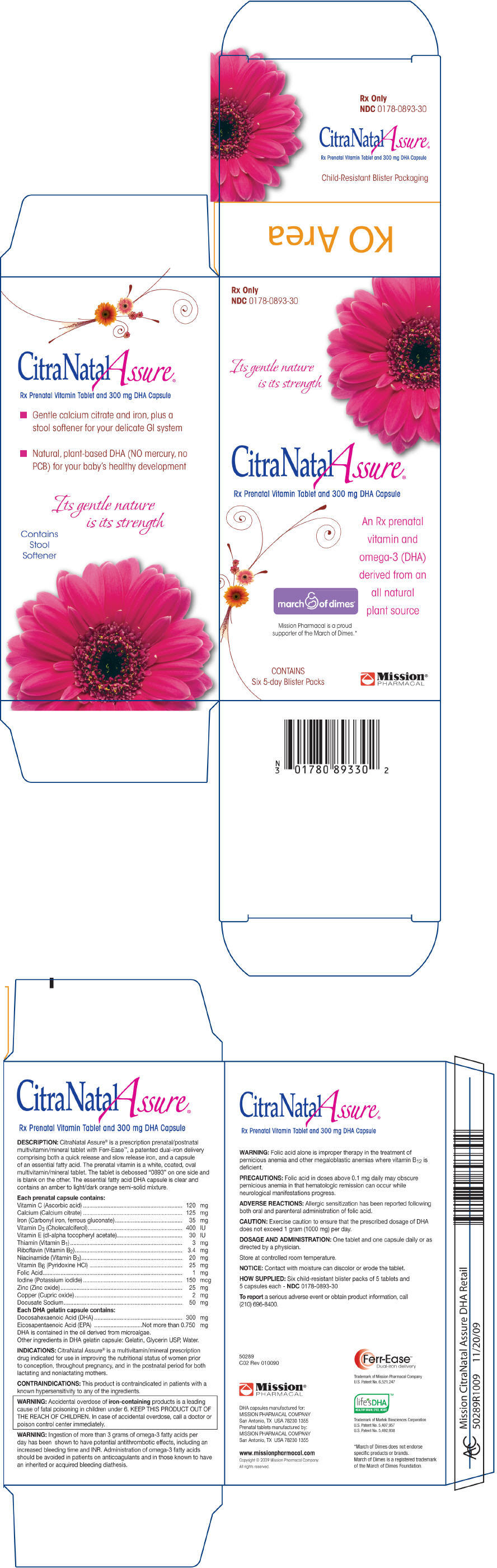 DRUG LABEL: CitraNatal Assure
NDC: 0178-0893 | Form: KIT | Route: ORAL
Manufacturer: Mission Pharmacal Company
Category: prescription | Type: HUMAN PRESCRIPTION DRUG LABEL
Date: 20110519

ACTIVE INGREDIENTS: ascorbic acid 120 mg/1 1; calcium citrate 125 mg/1 1; Iron  35 mg/1 1; Cholecalciferol 400 [iU]/1 1; ALPHA-TOCOPHEROL 30 [iU]/1 1; Thiamine 3 mg/1 1; Riboflavin 3.4 mg/1 1; Niacinamide 20 mg/1 1; Pyridoxine Hydrochloride 25 mg/1 1; Folic Acid 1 mg/1 1; Iodine 150 ug/1 1; Zinc 25 mg/1 1; Copper 2 mg/1 1; Docusate Sodium 50 mg/1 1; DOCONEXENT 300 mg/1 1; ICOSAPENT 0.75 mg/1 1
INACTIVE INGREDIENTS: POVIDONE K30; Croscarmellose Sodium; Titanium Dioxide; Magnesium Silicate; Magnesium Stearate; Shellac; VANILLIN; Gelatin; Glycerin; Water

CitraNatalAssure®
Rx Prenatal Vitamin Tablet and 300 mg DHA Capsule

DESCRIPTION

CitraNatal Assure® is a prescription prenatal/postnatal multivitamin/mineral tablet with Ferr-Ease™, a patented dual-iron delivery comprising both a quick release and slow release iron, and a capsule of an essential fatty acid. The prenatal vitamin is a white, coated, oval multivitamin/mineral tablet. The tablet is debossed "0893" on one side and is blank on the other. The essential fatty acid DHA capsule is clear and contains an amber to light/dark orange semi-solid mixture.

Each prenatal capsule contains:
Vitamin C (Ascorbic acid) | 120 | mg
Calcium (Calcium citrate) | 125 | mg
Iron (Carbonyl iron, ferrous gluconate) | 35 | mg
Vitamin D3 (Cholecalciferol) | 400 | IU
Vitamin E (dl-alpha tocopheryl acetate) | 30 | IU
Thiamin (Vitamin B1) | 3 | mg
Riboflavin (Vitamin B2) | 3.4 | mg
Niacinamide (Vitamin B3) | 20 | mg
Vitamin B6 (Pyridoxine HCl) | 25 | mg
Folic Acid | 1 | mg
Iodine (Potassium iodide) | 150 | mcg
Zinc (Zinc oxide) | 25 | mg
Copper (Cupric oxide) | 2 | mg
Docusate Sodium | 50 | mg
Each DHA gelatin capsule contains:
Docosahexaenoic Acid (DHA) | 300 | mg
Eicosapentaenoic Acid (EPA) | Not more than 0.750 | mg

DHA is contained in the oil derived from microalgae.

Other ingredients in DHA gelatin capsule: Gelatin, Glycerin USP, Water.

INDICATIONS

CitraNatal Assure® is a multivitamin/mineral prescription drug indicated for use in improving the nutritional status of women prior to conception, throughout pregnancy, and in the postnatal period for both lactating and nonlactating mothers.

CONTRAINDICATIONS

This product is contraindicated in patients with a known hypersensitivity to any of the ingredients.

WARNING

Accidental overdose of iron-containing products is a leading cause of fatal poisoning in children under 6. KEEP THIS PRODUCT OUT OF THE REACH OF CHILDREN. In case of accidental overdose, call a doctor or poison control center immediately.

WARNING

Ingestion of more than 3 grams of omega-3 fatty acids per day has been shown to have potential antithrombotic effects, including an increased bleeding time and INR. Administration of omega-3 fatty acids should be avoided in patients on anticoagulants and in those known to have an inherited or acquired bleeding diathesis.

WARNING

Folic acid alone is improper therapy in the treatment of pernicious anemia and other megaloblastic anemias where vitamin B12 is deficient.

PRECAUTIONS

Folic acid in doses above 0.1 mg daily may obscure pernicious anemia in that hematologic remission can occur while neurological manifestations progress.

ADVERSE REACTIONS

Allergic sensitization has been reported following both oral and parenteral administration of folic acid.

CAUTION

Exercise caution to ensure that the prescribed dosage of DHA does not exceed 1 gram (1000 mg) per day.

DOSAGE AND ADMINISTRATION

One tablet and one capsule daily or as directed by a physician.

STORAGE AND HANDLING

Store at controlled room temperature.

NOTICE

Contact with moisture can discolor or erode the tablet.

HOW SUPPLIED

Six child-resistant blister packs of 5 tablets and 5 capsules each - NDC 0178-0893-30

To report a serious adverse event or obtain product information, call (210) 696-8400.

50289
C02 Rev 010090

Mission®
PHARMACAL

DHA capsules manufactured for:
MISSION PHARMACAL COMPANY
San Antonio, TX USA 78230 1355
Prenatal tablets manufactured by:
MISSION PHARMACAL COMPANY
San Antonio, TX USA 78230 1355

www.missionpharmacal.com

Copyright © 2009 Mission Pharmacal Company.

All rights reserved.

Ferr-Ease™
Dual-iron delivery

Trademark of Mission Pharmacal Company
U.S. Patent No. 6,521,247

life's DHA™
HEALTHY BRAIN, EYES, HEART

Trademark of Martek Biosciences Corporation
U.S. Patent No. 5,407,957
U.S. Patent No. 5,492,938

*March of Dimes does not endorse
specific products or brands.
March of Dimes is a registered trademark
of the March of Dimes Foundation.

PRINCIPAL DISPLAY PANEL - Six 5-day Blister Pack Carton

Rx Only
NDC 0178-0893-30

Its gentle nature
is its strength

CitraNatalAssure®

Rx Prenatal Vitamin Tablet and 300 mg DHA Capsule

An Rx prenatal
vitamin and
omega-3 (DHA)
derived from an
all natural
plant source

march of dimes®

Mission Pharmacal is a proud
supporter of the March of Dimes.*

CONTAINS
Six 5-day Blister Packs

Mission®
PHARMACAL